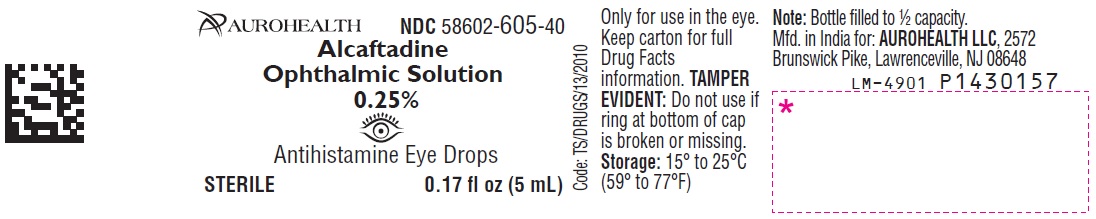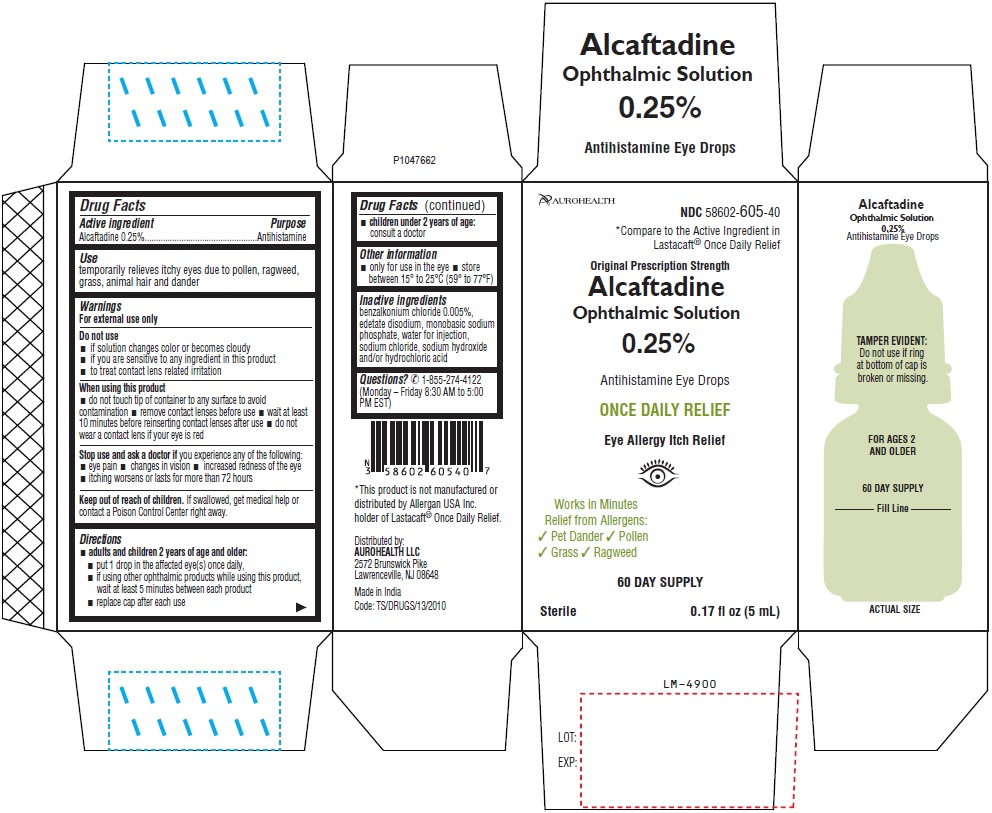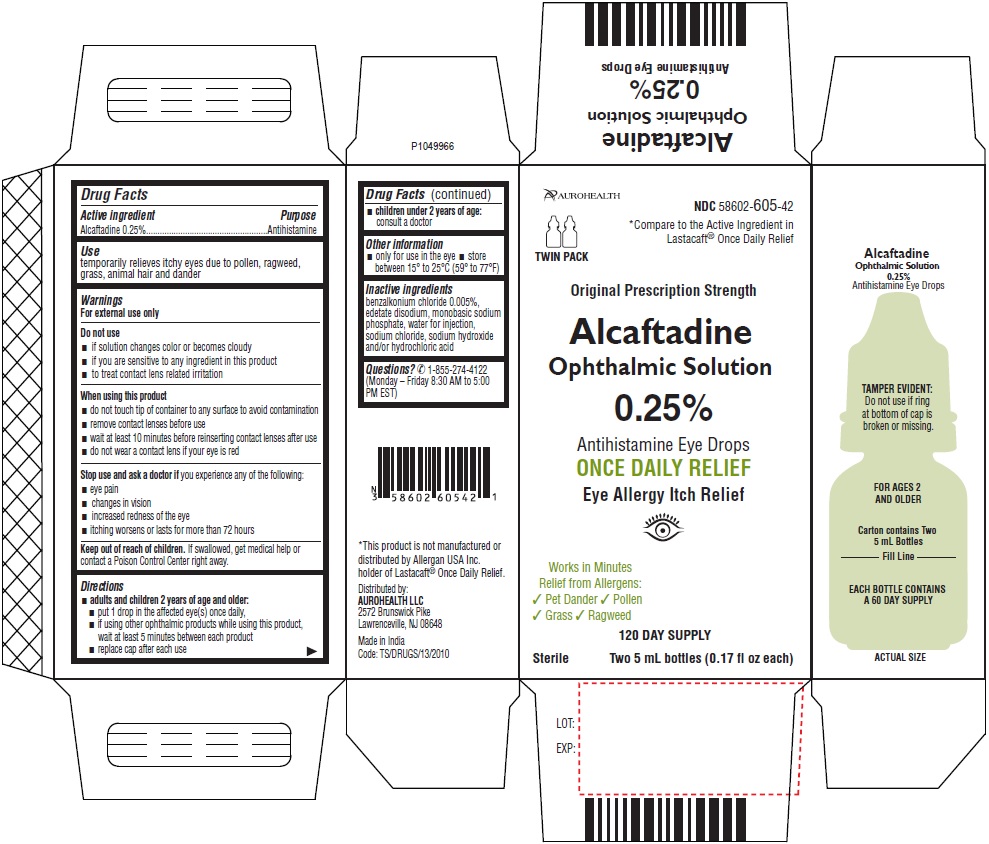 DRUG LABEL: Alcaftadine
NDC: 58602-605 | Form: SOLUTION/ DROPS
Manufacturer: Aurohealth LLC
Category: otc | Type: Human OTC Drug Label
Date: 20230623

ACTIVE INGREDIENTS: ALCAFTADINE 2.5 mg/1 mL
INACTIVE INGREDIENTS: BENZALKONIUM CHLORIDE; EDETATE DISODIUM; HYDROCHLORIC ACID; SODIUM PHOSPHATE, MONOBASIC; SODIUM CHLORIDE; SODIUM HYDROXIDE; WATER

Drug Facts

Active ingredient
Alcaftadine 0.25%

Purpose

Antihistamine

Use

temporarily relieves itchy eyes due to pollen, ragweed, grass, animal hair and dander

Warnings

For external use only

Do not use

- if solution changes color or becomes cloudy
- if you are sensitive to any ingredient in this product
- to treat contact lens related irritation

When using this product

- do not touch tip of container to any surface to avoid contamination
- remove contact lenses before use
- wait at least 10 minutes before reinserting contact lenses after use
- do not wear a contact lens if your eye is red

Stop use and ask a doctor if

you experience any of the following:

- eye pain
- changes in vision
- increased redness of the eye
- itching worsens or lasts for more than 72 hours

Keep out of reach of children.

If swallowed, get medical help or contact a Poison Control Center right away.

Directions

- adults and children 2 years of age and older:
  - put 1 drop in the affected eye(s) once daily,
  - if using other ophthalmic products while using this product, wait at least 5 minutes between each product
  - replace cap after each use
- children under 2 years of age:
  - consult a doctor

Other information

- only for use in the eye
- store between 15° to 25°C (59° to 77°F)

Inactive ingredients

benzalkonium chloride 0.005%, edetate disodium, monobasic sodium phosphate, water for injection, sodium chloride, sodium hydroxide and/or hydrochloric acid

Questions?

✆1-855-274-4122
(Monday – Friday 8:30 AM to 5:00 PM EST).

Distributed by:
AUROHEALTH LLC
2572 Brunswick Pike
Lawrenceville, NJ 08648

Made in India
Revised: May 2023

PACKAGE LABEL-PRINCIPAL DISPLAY PANEL-0.25 % (5 mL Container Label)

AUROHEALTH NDC 58602-605-40
Alcaftadine
Ophthalmic Solution
0.25%
Antihistamine Eye Drops
STERILE 0.17 fl oz (5 mL)

PACKAGE LABEL-PRINCIPAL DISPLAY PANEL-0.25% (5 mL Container-Carton)

AUROHEALTH NDC 58602-605-40
*Compare to the Active Ingredient in
Lastacaft® Once Daily Relief
Original Prescription Strength
Alcaftadine
Ophthalmic Solution
0.25%
Antihistamine Eye Drops
ONCE DAILY RELIEF
Eye Allergy Itch Relief
Works in Minutes
Relief from Allergens:
✓ Pet Dander ✓ Pollen
✓ Grass ✓ Ragweed
60 DAY SUPPLY
Sterile 0.17 fl oz (5 mL)

PACKAGE LABEL-PRINCIPAL DISPLAY PANEL-0.25% (5 mL Container-Carton) Twin Pack

AUROHEALTH NDC 58602-605-42
*Compare to the Active Ingredient in
Lastacaft® Once Daily Relief
TWIN PACK
Original Prescription Strength
Alcaftadine
Ophthalmic Solution
0.25%
Antihistamine Eye Drops
ONCE DAILY RELIEF
Eye Allergy Itch Relief
Works in Minutes
Relief from Allergens:
✓ Pet Dander ✓ Pollen
✓ Grass ✓ Ragweed
120 DAY SUPPLY
Sterile Two 5 mL bottles (0.17 fl oz each)